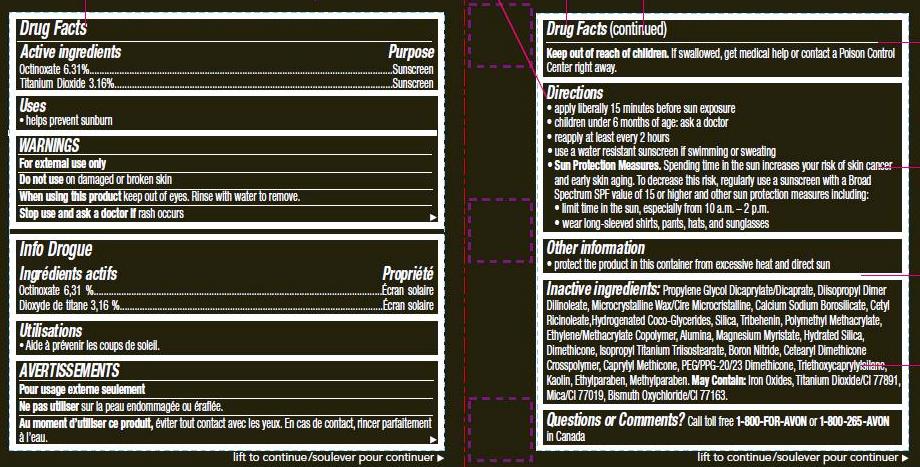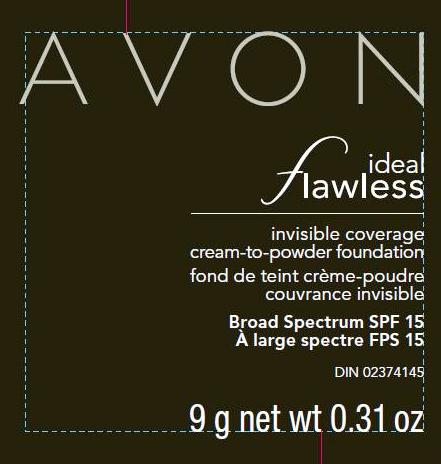 DRUG LABEL: ideal flawless
NDC: 10096-0279 | Form: CREAM
Manufacturer: New Avon LLC
Category: otc | Type: HUMAN OTC DRUG LABEL
Date: 20160209

ACTIVE INGREDIENTS: OCTINOXATE	 63.1 mg/1 g; TITANIUM DIOXIDE	 31.6 mg/1 g

Active Ingredients
Octinoxate 6.31%................................................
Titanium Dioxide 3.16%.......................................

Purpose
................ Sunscreen
................ Sunscreen

Uses
■ helps prevent sunburn

WARNINGS
For external use only

Do not use on damaged or broken skin

When using this product keep out of eyes. Rinse with water to remove.

Stop use and ask a doctor if rash occurs

Keep out of reach of children. If swallowed, get medical help or
contact a Poison Control Center right away.

Directions
• apply liberally 15 minutes before sun exposure
• children under 6 months of age: ask a doctor
• reapply at least every 2 hours
• use a water resistant sunscreen if swimming or sweating
• Sun Protection Measures. Spending time in the sun increases your risk of skin cancer
and early skin aging. To decrease this risk, regularly use a sunscreen with a Broad
Spectrum SPF value of 15 or higher and other sun protection measures including:
• limit time in the sun, especially from 10 a.m. – 2 p.m.
• wear long-sleeved shirts, pants, hats, and sunglasses

Other Information
■ protect the product in this container from excessive heat and direct sun.

INACTIVE INGREDIENT

Inactive ingredients: Propylene Glycol Dicaprylate/Dicaprate, Diisopropyl Dimer Dilinoleate, Microcrystalline Wax/Cire Microcristalline, Calcium Sodium Borosilicate, Cetyl Ricinoleate,Hydrogenated Coco-Glycerides, Silica, Tribehenin, Polymethyl Methacrylate, Ethylene/Methacrylate Copolymer, Alumina, Magnesium Myristate, Hydrated Silica, Dimethicone, Isopropyl Titanium Triisostearate, Boron Nitride, Cetearyl Dimethicone Crosspolymer, Caprylyl Methicone, PEG/PPG-20/23 Dimethicone, Triethoxycaprylylsilane, Kaolin, Ethylparaben, Methylparaben. May Contain: Iron Oxides, Titanium Dioxide/CI 77891, Mica/CI 77019, Bismuth Oxychloride/CI 77163.

Questions or Comments? Call toll free 1-800-FOR-AVON or 1-800-265-AVON
in Canada